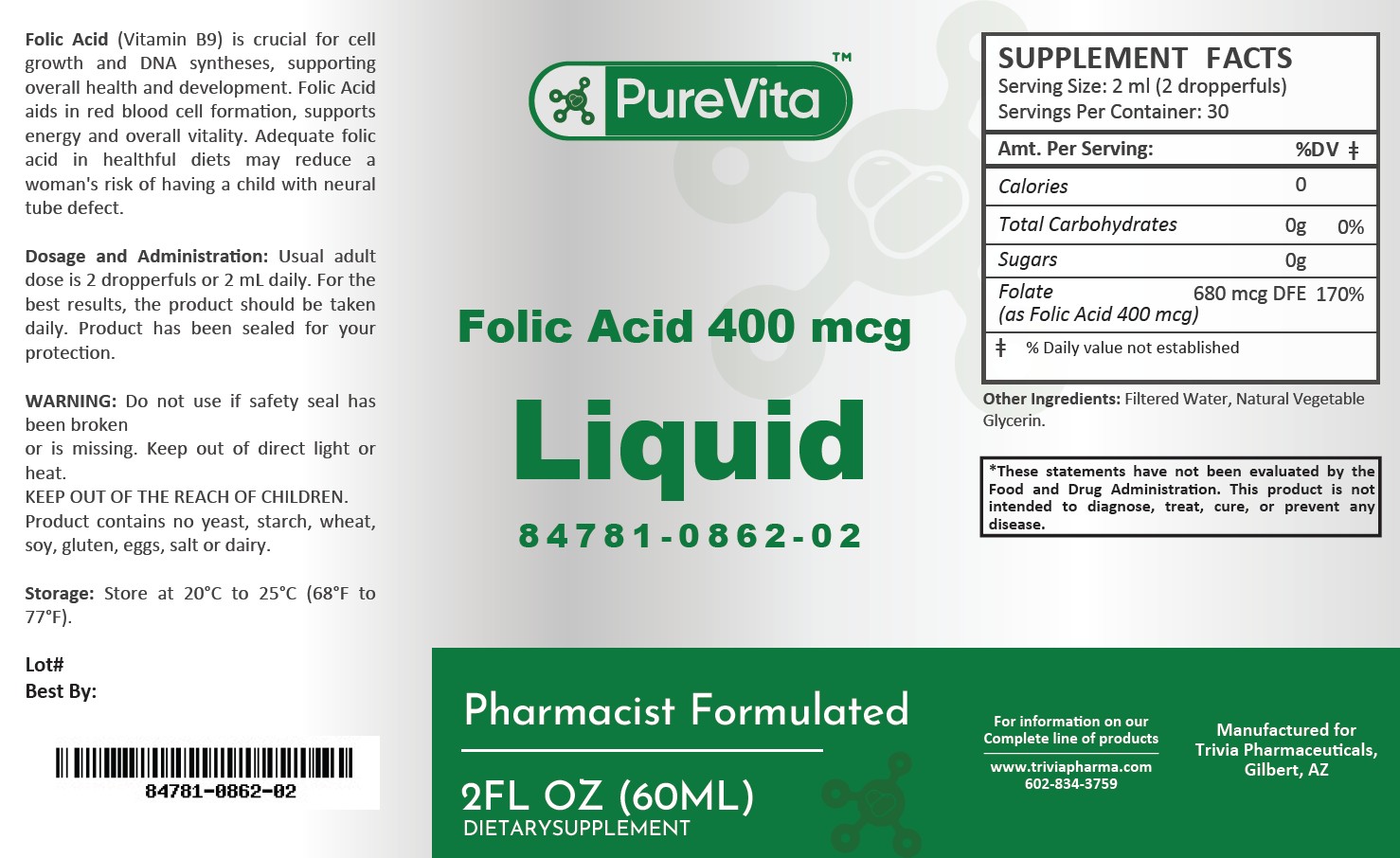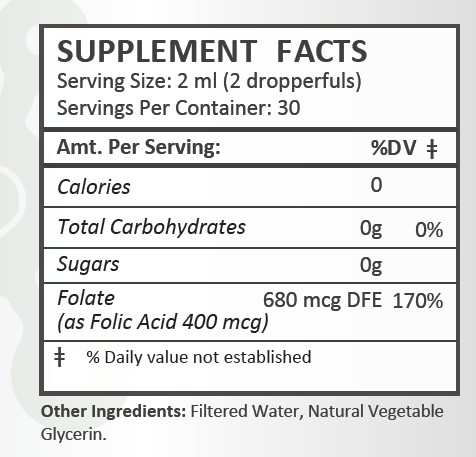 DRUG LABEL: PureVita Folic Acid 400 mcg
NDC: 84781-862 | Form: LIQUID
Manufacturer: Trivia Pharmaceuticals
Category: other | Type: Dietary Supplement
Date: 20250307

ACTIVE INGREDIENTS: FOLIC ACID 400 ug/2 mL

PureVita Folic Acid 400 mcg

Health Claim:

PureVita Folic Acid 400 mcg Liquid

Description:

PureVita Folic Acid 400 mcg liquid is an orally administered Folic Acid formulation. Folic Acid (Vitamin B9) is crucial for cell growth and DNA syntheses, supporting overall health and development. Folic Acid adis in red blood cell formation, supports energy and overall vitality. Adequate folic acid in healthful diets may reduce a woman's risk of having a child with neural tube defect.

This listed product is not a National Drug Code, but instead has merely been formatted to comply with standard industry practice for pharmacy and insurance computer systems.

Warnings:

Do not use if safety seal has been broken or is missing. Keep out of direct light or heat.

KEEP OUT OF THE REACH OF CHILDREN.

Product contains no yeast, starch, wheat, soy, gluten, eggs, salt or dairy.

Dosage and Adminsitration:

Usual adult dose is 2 dropperfuls or 2 mL daily. For the best results, the product should be taken daily. Product has been sealed for your protection.

How Supplied:

PureVita Folic Acid 400 mcg Liquid is supplied as yellow liquid.

84781-0862-02

Reserved for Professional Recommendation

All prescriptions using this product shall be pursuant to state statutes as applicable. This is not an Orange Book product. There are no implied or explicit claims on therapeutic equivalence.

Manufactured for:
Trivia Pharmaceuticals

Gilbert, AZ

Storage:

Storage: Store at 20^0C to 25^0C (68^0F to 77^0F). Keep refrigerated after opening.